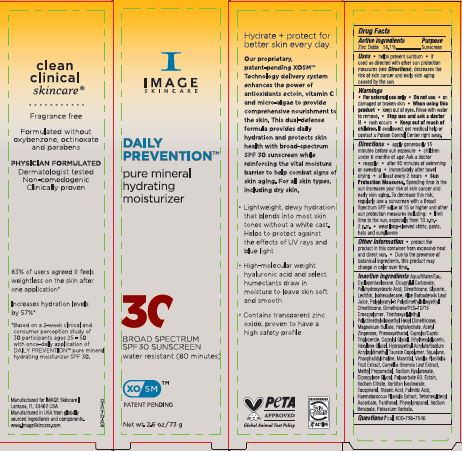 DRUG LABEL: Daily Prevention Pure Mineral Hydrating Moisturizer SPF30
NDC: 62742-4245 | Form: CREAM
Manufacturer: Allure Labs
Category: otc | Type: HUMAN OTC DRUG LABEL
Date: 20240222

ACTIVE INGREDIENTS: ZINC OXIDE 18.1 g/100 g
INACTIVE INGREDIENTS: STEARIC ACID; POLYHYDROXYSTEARIC ACID (2300 MW); MEDIUM-CHAIN TRIGLYCERIDES; ISOHEXADECANE; TRIETHOXYSILYLETHYL POLYDIMETHYLSILOXYETHYL HEXYL DIMETHICONE; POLYGLYCERYL-3 POLYDIMETHYLSILOXYETHYL DIMETHICONE (4000 MPA.S); POLYSORBATE 60; SORBITAN ISOSTEARATE; PALMITIC ACID; TETRAHEXYLDECYL ASCORBATE; PHENOXYETHANOL; ACETYL ZINGERONE; HEXYLENE GLYCOL; MANNITOL; VANILLA; POTASSIUM SORBATE; TOCOPHEROL; WATER; DIMETHICONE/PEG-10/15 CROSSPOLYMER; MAGNESIUM SULFATE HEPTAHYDRATE; HYDROXYETHYL ACRYLATE/SODIUM ACRYLOYLDIMETHYL TAURATE COPOLYMER (45000 MPA.S AT 1%); LECITHIN, SOYBEAN; ALOE VERA LEAF; HAEMATOCOCCUS PLUVIALIS; PHENYLPROPANOL; SODIUM BENZOATE; SODIUM CITRATE; DICAPRYLYL CARBONATE; HYALURONATE SODIUM; CYCLOMETHICONE 5; DIMETHICONE; GLYCERIN; ETHYLHEXYLGLYCERIN; METHYLPROPANEDIOL; PANTHENOL; SQUALANE; PHOSPHATIDYLCHOLINE TRANSLOCATOR ABCB4; GREEN TEA LEAF; ECTOINE

Drug Facts

Active ingredients :

Zinc Oxide 18.1%

Purpose:

Sunscreen

INDICATIONS AND USAGE

Uses • helps prevent sunburn • if used as directed with other sun protection measures (see Directions), decreases the risk of skin cancer and early skin aging caused by the sun

Warnings • For external use only

Do not use on damaged or broken skin

When using this product keep out of eyes. Rinse with water to remove.

Stop use and ask a doctor if rash occurs

Keep out of reach of children. If swallowed, get medical help or contact a Poison Control Center right away.

DOSAGE AND ADMINISTRATION

Directions • apply generously 15 minutes before sun exposure • children under 6 months of age: Ask a doctor • reapply after 80 minutes of swimming or sweating • immediately after towel drying • at least every 2 hours

• Sun Protection Measures. Spending time in the sun increases your risk of skin cancer and early skin aging. To decrease this risk, regularly use a sunscreen with a Broad Spectrum SPF value of 15 or higher and other sun protection measures including: • limit time in the sun, especially from 10 a.m.-2 p.m. • wear long-sleeved shirts, pants, hats and sunglasses

Other information • protect the product in this container from excessive heat and direct sun • Due to the presence of botanical ingredients , this product may change in color over time.

INACTIVE INGREDIENT

Water /Aqua/Eau, Cyclopentasiloxane, Dicaprylyl Carbonate, Polyhydroxystearic Acid, Dimethicone, Glycerin, Lecithin, Isohexadecane, Aloe Barbadensis Leaf Juice, Polyglyceryl-3 Polydimethylsiloxyethyl Dimethicone, Dimethicone/PEG-10/15 Crosspolymer, Triethoxysilylethyl Polydimethylsiloxyethyl Hexyl Dimethicone, Magnesium Sulfate Heptahydrate, Acetyl Zingerone, Phenoxyethanol, Caprylic/Capric Triglyceride, Caprylyl Glycol, Ethylhexylglycerin, Hexylene Glycol, Hydroxyethyl Acrylate/Sodium Acryloyldimethyl Taurate Copolymer, Squalane, Phosphatidylcholine, Mannitol, Vanilla Planifolia Fruit Extract, Camellia Sinensis Leaf Extract, Methyl Propanediol, Sodium Hyaluronate, Polysorbate 60,Ectoin,Sodium Citrate,Sorbitan Isostearate, Tocopherol, Stearic Acid, Palmitic Acid, Haematococcus Pluvialis Extract, Tetrahexyldecyl Ascorbate, Panthenol, Phenylpropanol, Sodium Benzoate, Potassium Sorbate